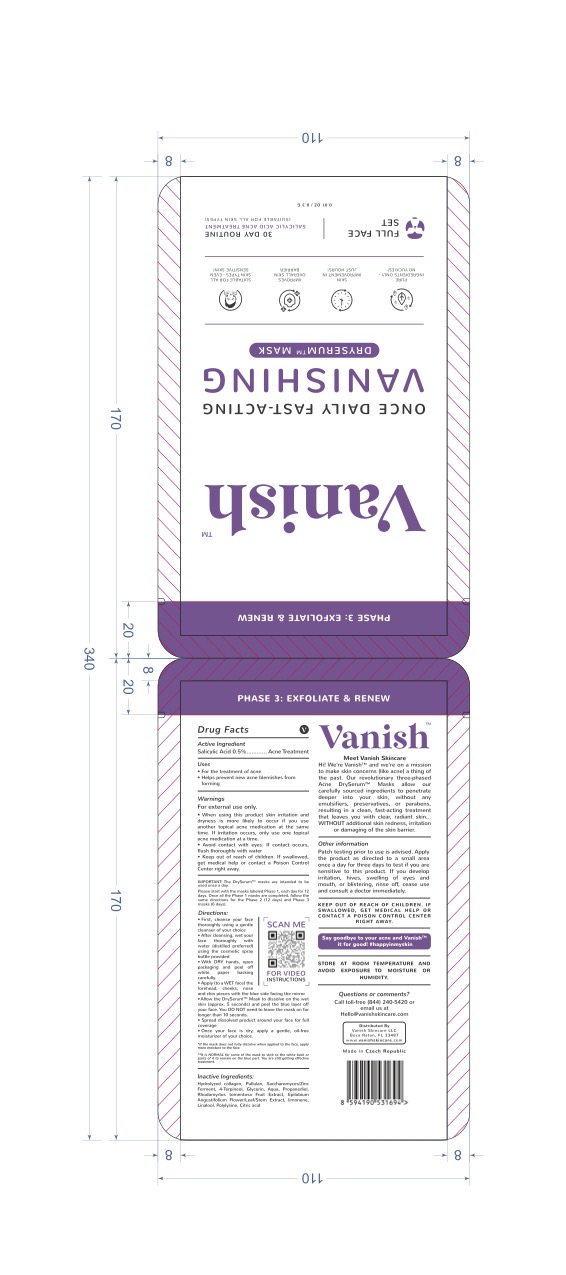 DRUG LABEL: Vanishing Skincare
NDC: 85059-001 | Form: PATCH
Manufacturer: Vanish Skincare LLC
Category: otc | Type: HUMAN OTC DRUG LABEL
Date: 20251128

ACTIVE INGREDIENTS: SALICYLIC ACID 0.5 mg/100 mg
INACTIVE INGREDIENTS: GLYCERIN

Active Ingredient(s)

Active Ingredient: Salicylic Acid 0.5%.

Warning Section

For external use only. Avoid contact with eyes. If contact occurs, rinse thoroughly with water. Stop use and ask a doctor if rash or irritation occurs. Keep out of reach of children. If swallowed, get medical help or contact a Poison Control Center right away.

Dosage

Apply a thin, even layer to clean, dry skin. Leave on for 10–15 minutes. Rinse thoroughly with warm water. Use 1–2 times per week or as directed by a healthcare provider."

INACTIVE INGREDIENT

Water, Glycerin, Aloe Vera Leaf Juice, Lactic Acid, Glycolic Acid, Kaolin, Citric Acid, Fragrance.

INDICATIONS AND USAGE

Helps exfoliate and renew skin for a smoother, brighter appearance. Hydrates and improves skin texture.

Keep out of reach of children. If swallowed, get medical help or contact a Poison Control Center right away.

PURPOSE

Exfoliation and skin renewal.

DOSAGE AND ADMINISTRATION

1. Cleanse face thoroughly. 2. Apply the mask to dry skin, avoiding contact with eyes. 3. Leave on for 15-20 minutes andremove gently. 4. Use once or twice a week as needed.

PACKAGE LABEL

See attached image for the Principal Display Panel.